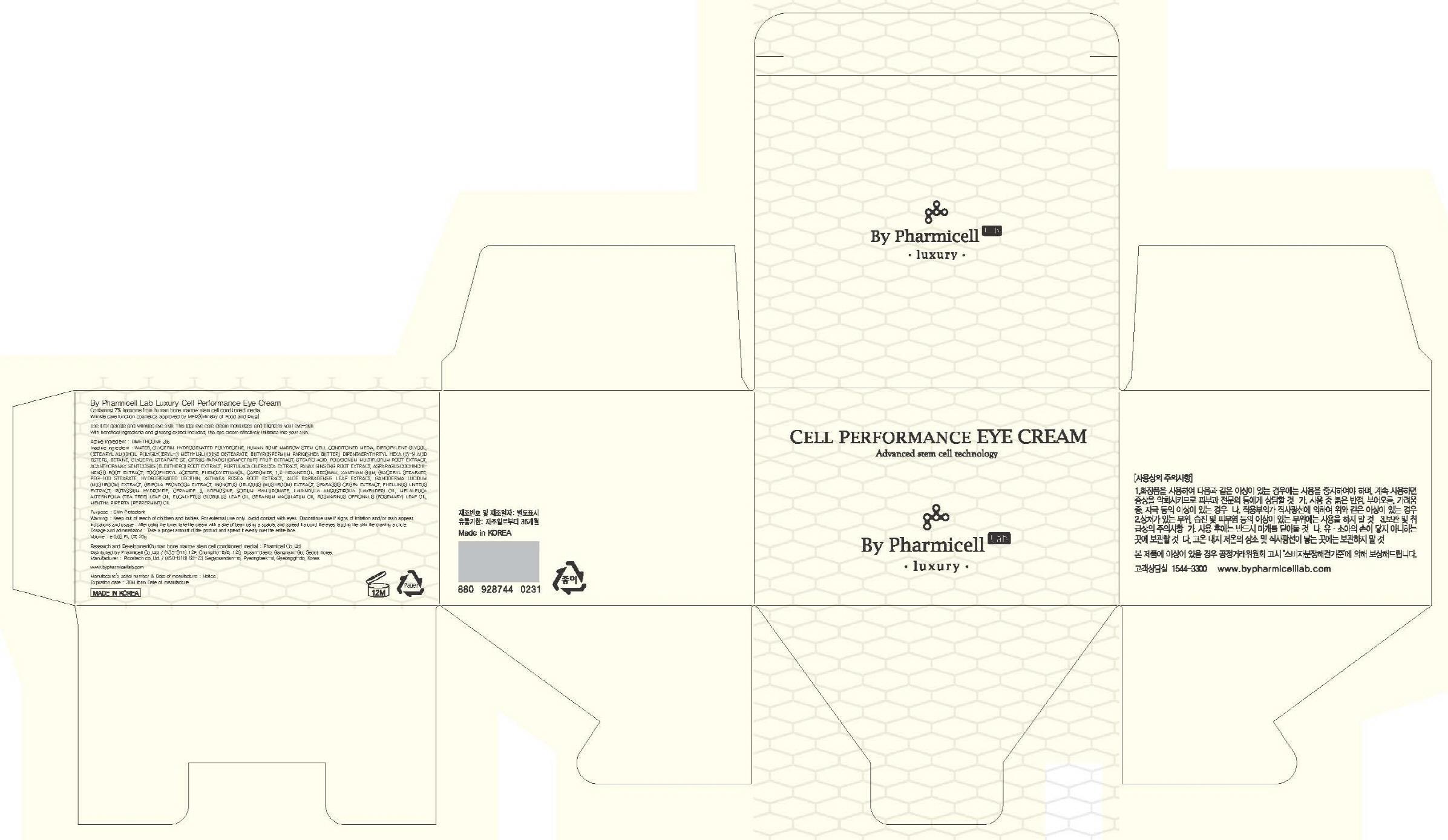 DRUG LABEL: By Pharmicell Lab Luxury Cell Performance Eye
NDC: 60949-070 | Form: CREAM
Manufacturer: Pharmicell Co., Ltd.
Category: otc | Type: HUMAN OTC DRUG LABEL
Date: 20130707

ACTIVE INGREDIENTS: DIMETHICONE 0.6 g/20 g
INACTIVE INGREDIENTS: WATER; GLYCERIN

ACTIVE INGREDIENT

Active ingredient : DIMETHICONE 3%

INACTIVE INGREDIENT

Inactive ingredient : WATER, GLYCERIN, HYDROGENATED POLYDECENE, HUMAN BONE MARROW STEM CELL CONDITIONED MEDIA, DIPROPYLENE GLYCOL, CETEARYL ALCOHOL, POLYGLYCERYL-3 METHYLGLUCOSE DISTEARATE, BUTYROSPERMUM PARKII(SHEA BUTTER), DIPENTAERYTHRITYL HEXA C5-9 ACID ESTERS, BETAINE, GLYCERYL STEARATE SE, CITRUS PARADISI (GRAPEFRUIT) FRUIT EXTRACT, STEARIC ACID, POLYGONUM MULTIFLORUM ROOT EXTRACT, ACANTHOPANAX SENTICOSUS (ELEUTHERO) ROOT EXTRACT, PORTULACA OLERACEA EXTRACT, PANAX GINSENG ROOT EXTRACT, ASPARAGUS COCHINCHINENSIS ROOT EXTRACT, TOCOPHERYL ACETATE, PHENOXYETHANOL, CARBOMER, 1,2-HEXANEDIOL, BEESWAX, XANTHAN GUM, GLYCERYL STEARATE, PEG-100 STEARATE, HYDROGENATED LECITHIN, ALTHAEA ROSEA ROOT EXTRACT, ALOE BARBADENSIS LEAF EXTRACT, GANODERMA LUCIDUM (MUSHROOM) EXTRACT, GRIFOLA FRONDOSA EXTRACT, INONOTUS OBLIQUUS (MUSHROOM) EXTRACT, SPARASSIS CRISPA EXTRACT, PHELLINUS LINTEUS EXTRACT, POTASSIUM HYDROXIDE, CERAMIDE 3, ADENOSINE, SODIUM HYALURONATE, LAVANDULA ANGUSTIFOLIA (LAVENDER) OIL, MELALEUCA ALTERNIFOLIA (TEA TREE) LEAF OIL, EUCALYPTUS GLOBULUS LEAF OIL, GERANIUM MACULATUM OIL, ROSMARINUS OFFICINALIS (ROSEMARY) LEAF OIL, MENTHA PIPERITA (PEPPERMINT) OIL

PURPOSE

Purpose : Skin Protectant

WARNINGS

Warning : Keep out of reach of children and babies. For external use only. Avoid contact with eyes. Discontinue use if signs of irritation and/or rash appear.

Keep out of reach of children and babies.

Indications and usage : After using the toner, take the cream with a size of bean using a spatula, and spread it around the eyes, tapping the skin like drawing a circle.

Dosage and administration : Take a proper amount of the product and spread it evenly over the entire face.